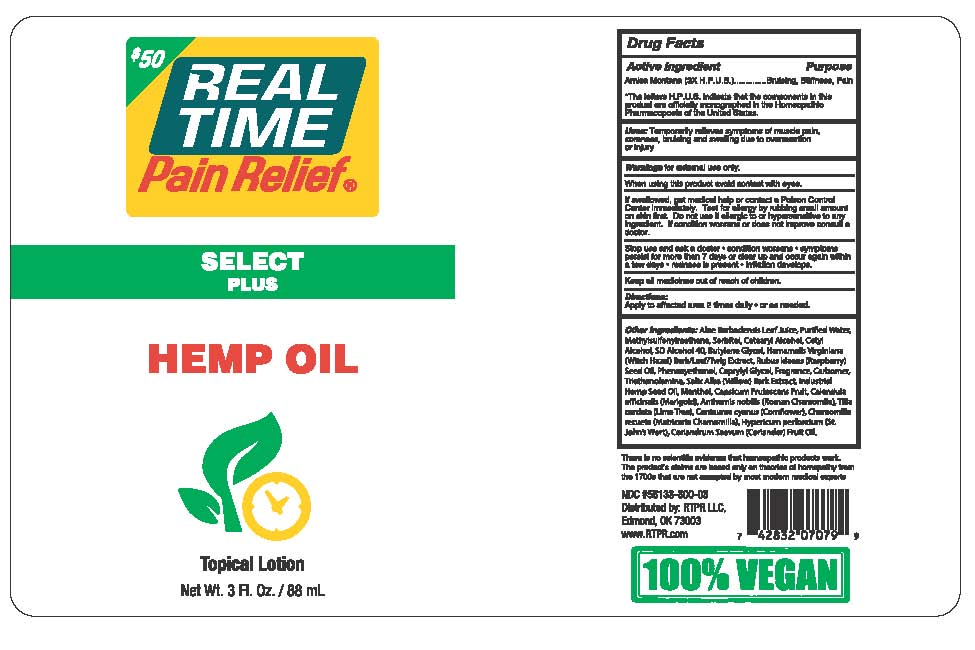 DRUG LABEL: Real Time Pain Relief Select Plus Hemp Oil
NDC: 58133-800 | Form: LOTION
Manufacturer: Cosmetic Specialty Labs, Inc.
Category: homeopathic | Type: HUMAN OTC DRUG LABEL
Date: 20180115

ACTIVE INGREDIENTS: ARNICA MONTANA 3 [hp_X]/1 mL
INACTIVE INGREDIENTS: ALOE VERA LEAF; DIMETHYL SULFONE; CETOSTEARYL ALCOHOL; TRIETHANOLAMINE TRIS(DIHYDROGEN PHOSPHATE); CALENDULA OFFICINALIS SEED OIL; TILIA CORDATA FLOWER; CENTAUREA CYANUS FLOWER; WATER; SORBITOL; CETYL ALCOHOL; HAMAMELIS VIRGINIANA ROOT BARK/STEM BARK; RUBUS IDAEUS SEED; PHENOXYETHANOL; CAPRYLYL GLYCOL; CARBOMER 940; SALIX ALBA BARK; HEMP; CAPSICUM FRUTESCENS WHOLE; HYPERICUM PERFORATUM; ALCOHOL; BUTYLENE GLYCOL; MENTHOL; CHAMOMILE; MATRICARIA CHAMOMILLA FLOWERING TOP OIL; CORIANDRUM SATIVUM WHOLE

Real Time Pain Relief Select Plus Hemp Oil

Active Ingredient

Arnica Montana (3X H.P.U.S.)

Purpose

Bruising, Stiffness, Pain

*The letters H.P.U.S. indicate that the components in this product are officially monographed in the Homeopathic Pharmacopoeia of the United States.

Uses

Temporarily relieves symptoms of muscle pain, soreness, bruising and swelling due to overexertion or injury.

Warnings

for external use only

When using this product

- avoid contact with eyes
- If swallowed, get medical help or contact a Poison Control Center immediately.
- Test for allergy by rubbing small amount on skin first.
- Do not use if allergic to or hypersensitive to any ingredient.
- If condition worsens or does not improve consult a doctor.

Stop use and ask a doctor if:

- condition worsens
- symptoms persist for more than 7 days or clear up and occur again within a few days
- redness is present
- irritation develops

Keep all medicines out of reach of children.

Directions:

Apply to affected area 2 times daily or as needed.

Other Ingredients:

Aloe Barbadensis Leaf Juice, Purified Water, Methylsulfonylmethane, Sorbitol, Cetearyl Alcohol, Cetyl Alcohol, SD Alcohol 40, Butylene Glycol, Hamamelic Virginiana (Witch Hazel) Bark/Leaf/Twig Extract, Rubus Idaeus (Raspberry) Seed Oil, Phenoxyethanol, Caprylyl Glycol, Fragrance, Carbomer, Triethanolamine, Salix Alba (Willow) Bark Extract, Industrial Hemp Seed Oil, Menthol, Capsicum Frutescens Fruit, Calendula officinalis (Marigold), Anthemis nobilis (Roman Chamomile), Tilia cordata (Lime Tree), Centaurea cyanus (Cornflower), Chamomilla recueta (Matricaria Chamomilla), Hypericum perforatum (St. John’s Wort), Coriandrum Saevum (Coriander) Fruit Oil.

There is no scientific evidence that homeopathic products work. The product’s claims are based only on theories of homeopathy from the 1700s that are not accepted by most modern medical experts.

100% VEGAN